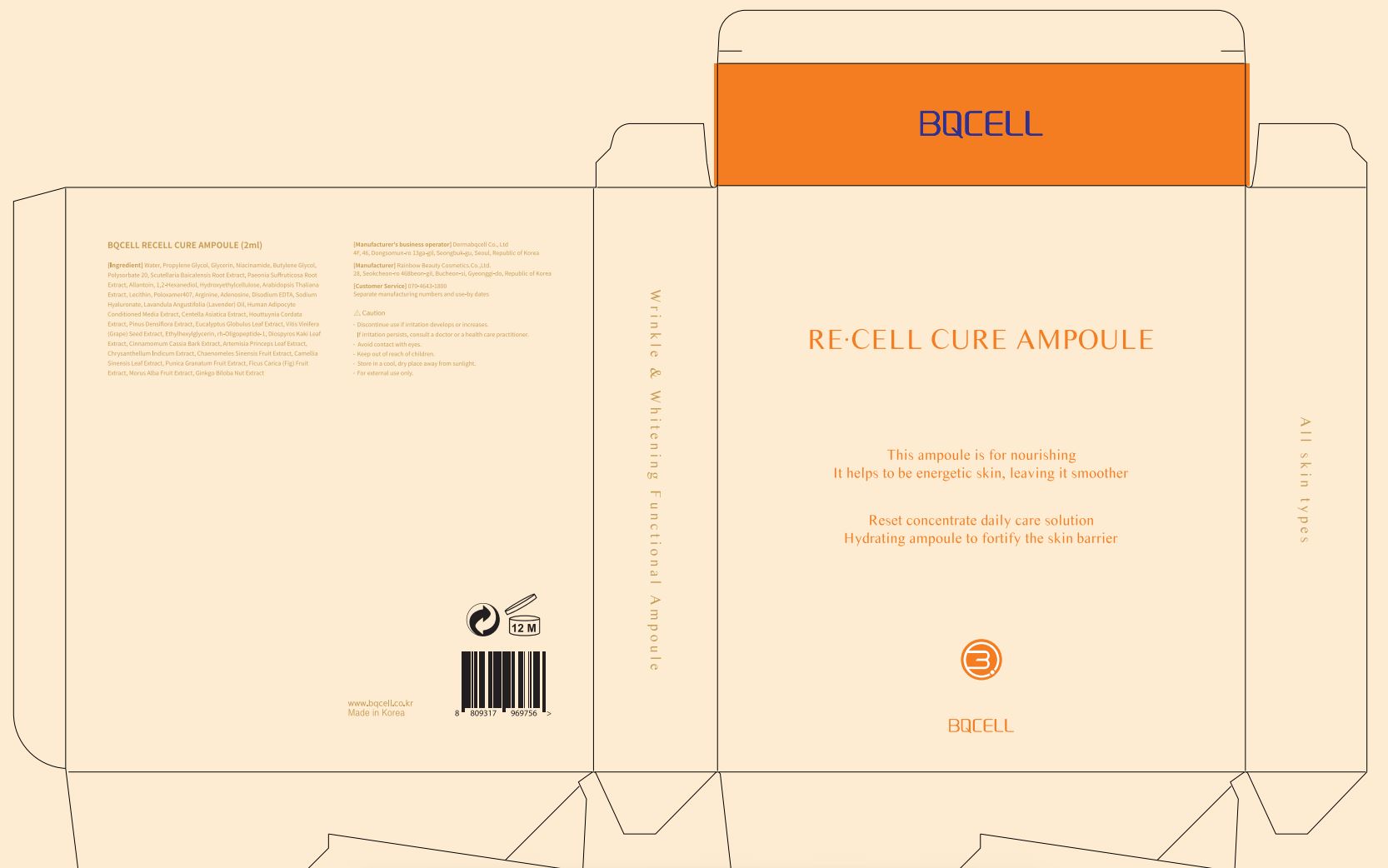 DRUG LABEL: RE CELL CURE AMPOULE
NDC: 82665-0002 | Form: LIQUID
Manufacturer: Dermabqcell Co., Ltd.
Category: otc | Type: HUMAN OTC DRUG LABEL
Date: 20221008

ACTIVE INGREDIENTS: ADENOSINE 2 g/100 mL; NIACINAMIDE 0.04 g/100 mL
INACTIVE INGREDIENTS: WATER

ACTIVE INGREDIENT

adenosine, niacinamide

INACTIVE INGREDIENT

Water, Propylene Glycol, Glycerin, Niacinamide, Butylene Glycol, Polysorbate 20,
Scutellaria Baicalensis Root Extract, Paeonia Suffruticosa Root Extract, Allantoin,
1,2-Hexanediol, Hydroxyethylcellulose, Arabidopsis Thaliana Extract, Lecithin,
Poloxamer407, Arginine, Adenosine, Disodium EDTA, Sodium Hyaluronate,
Lavandula Angustifolia (Lavender) Oil, Human Adipocyte Conditioned Media Extract,
Centella Asiatica Extract, Houttuynia Cordata Extract, Pinus Densiflora Extract,
Eucalyptus Globulus Leaf Extract, Vitis Vinifera (Grape) Seed Extract,
Ethylhexylglycerin, rh-Oligopeptide-1, Diospyros Kaki Leaf Extract, Cinnamomum
Cassia Bark Extract, Artemisia Princeps Leaf Extract, Chrysanthellum Indicum
Extract, Chaenomeles Sinensis Fruit Extract, Camellia Sinensis Leaf Extract, Punica
Granatum Fruit Extract, Ficus Carica (Fig) Fruit Extract, Morus Alba Fruit Extract,
Ginkgo Biloba Nut Extract

PURPOSE

wrinkle care, whitening

Keep out of reach of children

INDICATIONS AND USAGE

apply proper amount to the skin

WARNINGS

discontinue use if irritation develops or increases

if irritation persists, consult a doctor or a health care practitioner

avoid contact with eyes

keep out of reach of children

DOSAGE AND ADMINISTRATION

For external use only